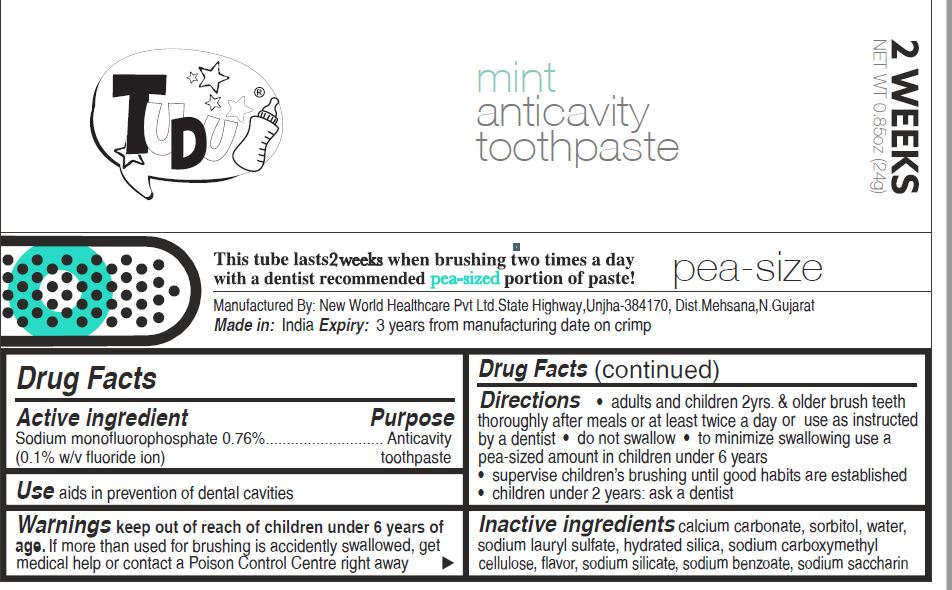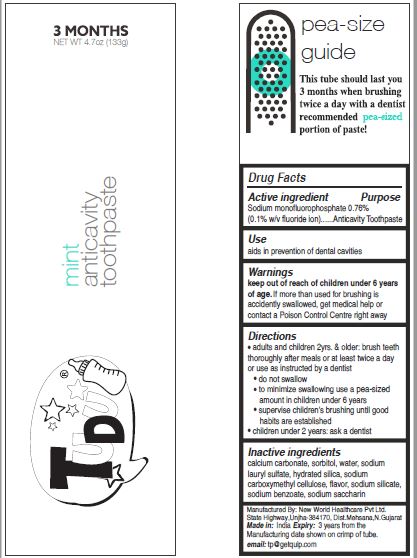 DRUG LABEL: NEWWORLD
NDC: 72423-0010 | Form: PASTE, DENTIFRICE
Manufacturer: NEW WORLD HEALTHCARE PRIVATE LIMITED
Category: otc | Type: HUMAN OTC DRUG LABEL
Date: 20180708

ACTIVE INGREDIENTS: SODIUM MONOFLUOROPHOSPHATE 0.76 g/100 g
INACTIVE INGREDIENTS: CALCIUM CARBONATE; SORBITOL; WATER; SODIUM LAURYL SULFATE; HYDRATED SILICA; CARBOXYMETHYLCELLULOSE SODIUM; SODIUM SILICATE; SODIUM BENZOATE; SACCHARIN SODIUM

Quip Anticavity Toothpaste

Drug Facts

Active ingredient

Sodium monofluorophosphate 0.76% (0.1% w/v fluoride ion)

Purpose

Anticavity toothpaste

Use

aids in prevention of dental cavities

Warnings

Keep out of reach of children under 6 years of age. If more than used for brushing is accidentally swallowed, get medical help or contact a Poison Control Centre right away.

Directions

- adults and children 2yrs. & older brush teeth thoroughly after meals or at least twice a day or use as instructed by a dentist
- do not swallow
- to minimize swallowing use a pea-sized amount in children under 6 years
- supervise children's brushing until good habits are established
- children under 2 years: ask a dentist

Inactive ingredients

calcium carbonate, sorbitol, water, sodium lauryl sulfate, hydrated silica, sodium carboxymethyl cellulose, flavor, sodium silicate, sodium benzoate, sodium saycharin